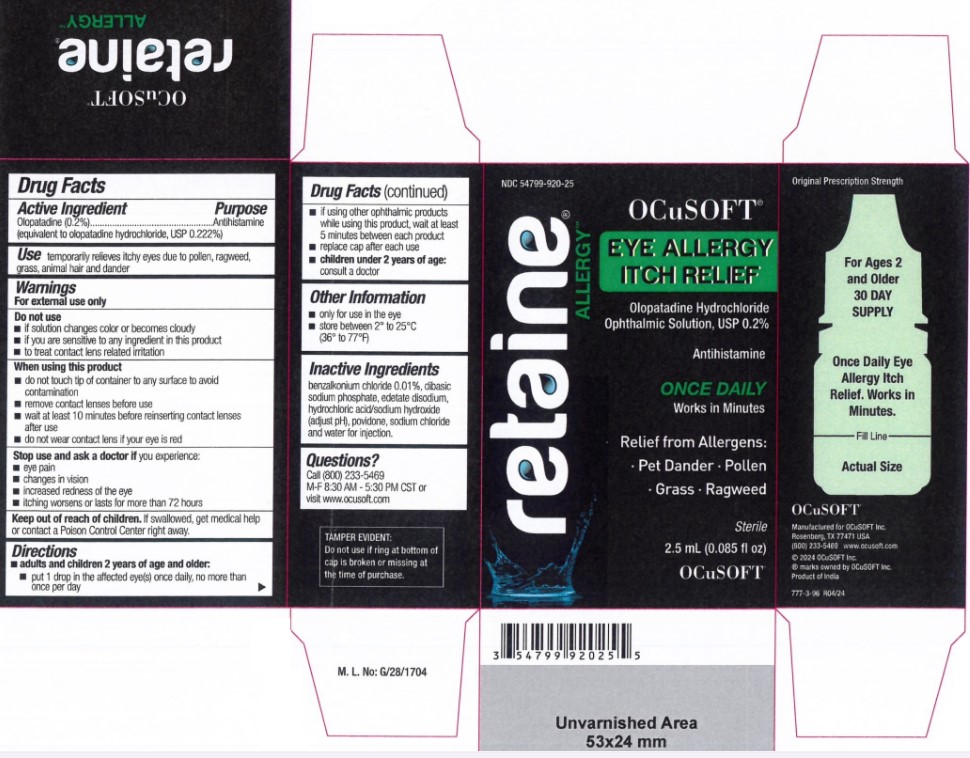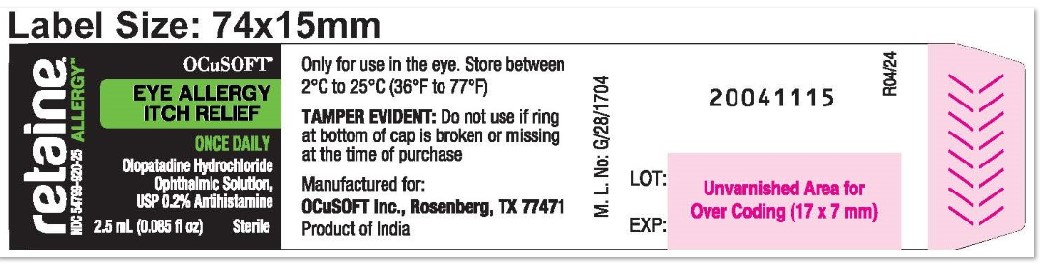 DRUG LABEL: Retaine Allergy
NDC: 54799-920 | Form: SOLUTION/ DROPS
Manufacturer: OCuSOFT INC.
Category: otc | Type: HUMAN OTC DRUG LABEL
Date: 20260107

ACTIVE INGREDIENTS: OLOPATADINE HYDROCHLORIDE 5 mg/2.5 mL
INACTIVE INGREDIENTS: Povidone, Unspecified; Sodium Phosphate, Dibasic, Unspecified Form; SODIUM CHLORIDE; EDETATE DISODIUM; BENZALKONIUM CHLORIDE; HYDROCHLORIC ACID; SODIUM HYDROXIDE; WATER

Drug Facts

Active Ingredient | Purpose
Olopatadine (0.2%)...................................... | Antihistamine
(equivalent to olopatadine hydrochloride, USP 0.222%)

Use

temporarily relieves itchy eyes due to pollen, ragweed, grass, animal hair and dander

Warnings

For external use only

Do not use

- if solution changes color or becomes cloudy
- if you are sensitive to any ingredient in this product
- to treat contact lens related irritation

When using this product

- do not touch tip of container to any surface to avoid contamination
- remove contact lenses before use
- wait at least 10 minutes before reinserting contact lenses after use
- do not wear contact lens if your eye is red

Stop use and ask a doctor if

you experience:

- eye pain
- changes in vision
- increased redness of the eye
- itching worsens or lasts for more than 72 hours

Keep out of reach of children.

If swallowed, get medical help or contact a Poison Control Center right away.

Directions

■ adults and children 2 years of age and older:

- put 1 drop in the affected eye(s) once daily, no more than once per day
- if using other ophthalmic products while using this product, wait at least 5 minutes between each product
- replace cap after each use

■ children under 2 years of age:
consult a doctor

Other Information

- only for use in the eye
- store between 2° to 25°C (36° to 77°F)

Inactive Ingredients

benzalkonium chloride 0.01%, dibasic sodium phosphate, edetate disodium, hydrochloric acid/sodium hydroxide (adjust pH), povidone, sodium chloride and water for injection.

Questions?

Call (800) 233-5469
M-F 8:30 AM - 5:30 PM CST or
visit www.ocusoft.com

PRINCIPAL DISPLAY PANEL

Retaine®
NDC-54799-25 ALLERGY
OCuSOFT
EYE ALLERGY
ITCH RELIEF
ONCE DAILY
Olopatadine Hydrochloride
Ophthalmic Solution,
USP 0.2% Antihistamine
2.5 mL (0.085 fl oz) Sterile
Only for use in the eye. Store between
2°C to 25°C (36°F to 77°F)
TAMPER EVIDENT: Do not use if ring
at bottom of cap is broken or missing
at the time of purchase
Manufactured for:
OCuSOFT Inc., Rosenberg, TX 77471
Product of India
M.L. No: G/28/1704
20041115
LOT:
EXP:
20041115
R04/24

Retaine®
ALLERGY
OCuSOFT®
Eye Allergy
Itch Relief
Olopatadine Hydrochloride
Ophthalmic Solution, USP 0.2%
Antihistamine
ONCE DAILY
Works in Minutes
Relief from Allergens:
· Pet Dander · Pollen
· Grass · Ragweed
Sterile
2.5mL (0.085 fl oz)
OCuSOFT
TAMPER EVIDENT:
Do not use if ring at bottom of
cap is broken or missing at
the time of purchase.
Original Prescription Strength
For Ages 2
and Older
30 DAY
SUPPLY
Once Daily Eye
Allergy Itch
Relief. Works in
Minutes.
Fill Line
Actual Size
OCuSOFT
Manufactured for OCuSOFT Inc.
Rosenberg, TX 77471 USA
(800) 233-5469 wwwocusoft.com
© 2024 OCuSOFT Inc.
® marks owned by OCuSOFT inc.
Product of India
777-3-96 R04/24